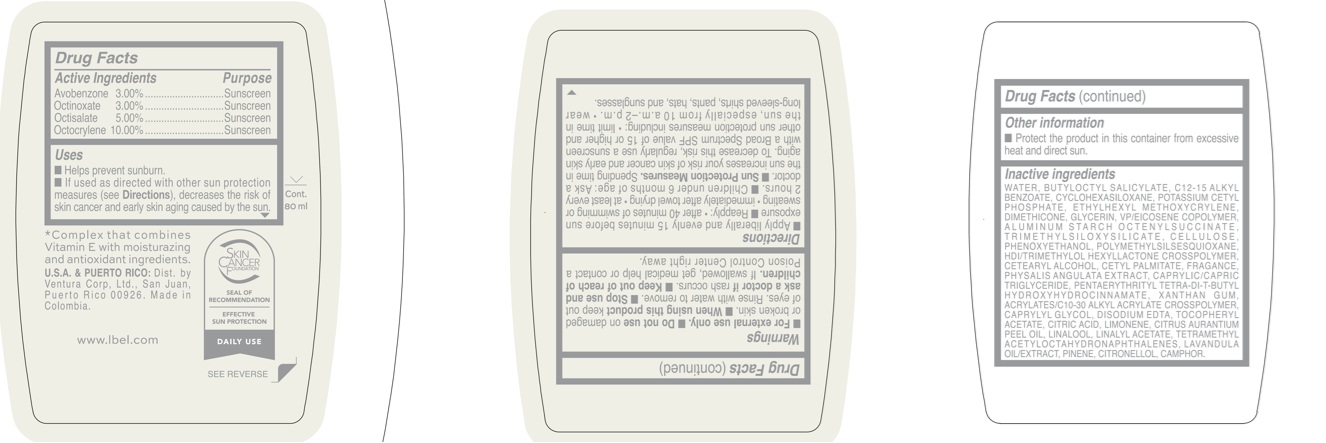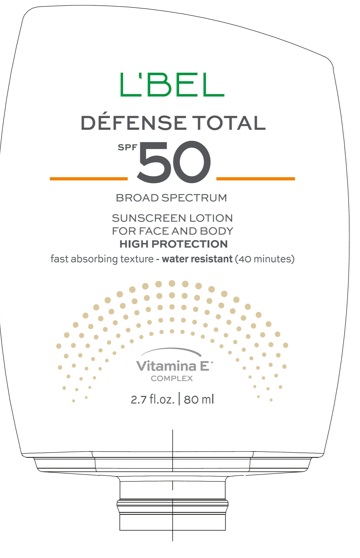 DRUG LABEL: LBEL DEFENSE TOTAL SUNSCREEN FOR FACE AND BODY SPF 50
NDC: 14141-405 | Form: EMULSION
Manufacturer: BEL STAR SA
Category: otc | Type: HUMAN OTC DRUG LABEL
Date: 20250428

ACTIVE INGREDIENTS: OCTOCRYLENE 100 mg/1 mL; OCTINOXATE 30 mg/1 mL; OCTISALATE 50 mg/1 mL; AVOBENZONE 30 mg/1 mL
INACTIVE INGREDIENTS: CETEARYL ALCOHOL; BUTYLOCTYL SALICYLATE; PENTAERYTHRITYL TETRA-DI-T-BUTYL HYDROXYHYDROCINNAMATE; PHENOXYETHANOL; ALUMINUM STARCH OCTENYLSUCCINATE; POLYMETHYLSILSESQUIOXANE (4.5 MICRONS); LINALYL ACETATE; TETRAMETHYL ACETYLOCTAHYDRONAPHTHALENES; ALPHA-TOCOPHEROL ACETATE; LINALOOL, (+)-; CAMPHOR (NATURAL); CITRONELLOL; ETHYLHEXYL METHOXYCRYLENE; CITRUS AURANTIUM PEEL OIL; EDETATE DISODIUM; WATER; XANTHAN GUM; PINENE; CYCLOHEXASILOXANE; POWDERED CELLULOSE; C12-15 ALKYL BENZOATE; CITRIC ACID; CETYL PALMITATE; PHYSALIS ANGULATA; CAPRYLIC/CAPRIC TRIGLYCERIDE; POTASSIUM CETYL PHOSPHATE; DIMETHICONE; EICOSYL POVIDONE; HDI/TRIMETHYLOL HEXYLLACTONE CROSSPOLYMER; ACRYLATES/C10-30 ALKYL ACRYLATE CROSSPOLYMER (60000 MPA.S); GLYCERIN; TRIMETHYLSILOXYSILICATE (M/Q 0.6-0.8); CAPRYLYL GLYCOL

LBEL DEFENSE TOTAL SUNSCREEN FOR FACE AND BODY SPF 50

Active Ingredients

Avobenzone 3.00%

Octinoxate 3.00%

Octisalate 5.00%

Octocrylene 10.00%

Purpose

Sunscreen

Uses

- Helps prevent sunburn.
- If used as directed with other sun protection measures (see Directions), decreases the risk of skin cancer and early skin aging caused by the sun.

Warnings

For external use only.

Do not use

on damaged or broken skin.

When using this product

keep out of eyes. Rinse with water to remove.

Stop use and ask a doctor if

rash occurs.

Keep out of reach of children.

If swallowed, get medical help or contact a Poison Control Center right away.

Directions

- Apply liberally and evenly 15 minutes before sun exposure.
- Reapply:
- after 40 minutes of swimming or sweating
- immediately after towel drying
- at least every 2 hours
- Children under 6 months of age: Ask a doctor
- Sun Protection Measures. Spending time in the sun increases your risk of skin cancer and early skin aging. To decrease this risk, regularly use a sunscreen with a Broad Spectrum SPF value of 15 or higher and other sun protection measures including:
- limit time in the sun, especially from 10 a.m.–2 p.m.
- wear long-sleeved shirts, pants, hats, and sunglasses.

Other information

- Protect the product in this container from excessive heat and direct sun.

Inactive ingredients

WATER, BUTYLOCTYL SALICYLATE, C12-15 ALKYL BENZOATE, CYCLOHEXASILOXANE, POTASSIUM CETYL PHOSPHATE, ETHYLHEXYL METHOXYCRYLENE, DIMETHICONE, GLYCERIN, VP/EICOSENE COPOLYMER, ALUMINUM STARCH OCTENYLSUCCINATE, TRIMETHYLSILOXYSILICATE, CELLULOSE, PHENOXYETHANOL, POLYMETHYLSILSESQUIOXANE, HDI/TRIMETHYLOL HEXYLLACTONE CROSSPOLYMER, CETEARYL ALCOHOL, CETYL PALMITATE, FRAGRANCE, PHYSALIS ANGULATA EXTRACT, CAPRYLIC/CAPRIC TRIGLYCERIDE, PENTAERYTHRITYL TETRA-DI-T-BUTYL HYDROXYHYDROCINNAMATE, XANTHAN GUM, ACRYLATES/C10-30 ALKYL ACRYLATE CROSSPOLYMER, CAPRYLYL GLYCOL, DISODIUM EDTA, TOCOPHERYL ACETATE, CITRIC ACID, LIMONENE, CITRUS AURANTIUM PEEL OIL, LINALOOL, LINALYL ACETATE, TETRAMETHYL ACETYLOCTAHYDRONAPHTHALENES, LAVANDULA OIL/EXTRACT, PINENE, CITRONELLOL, CAMPHOR.